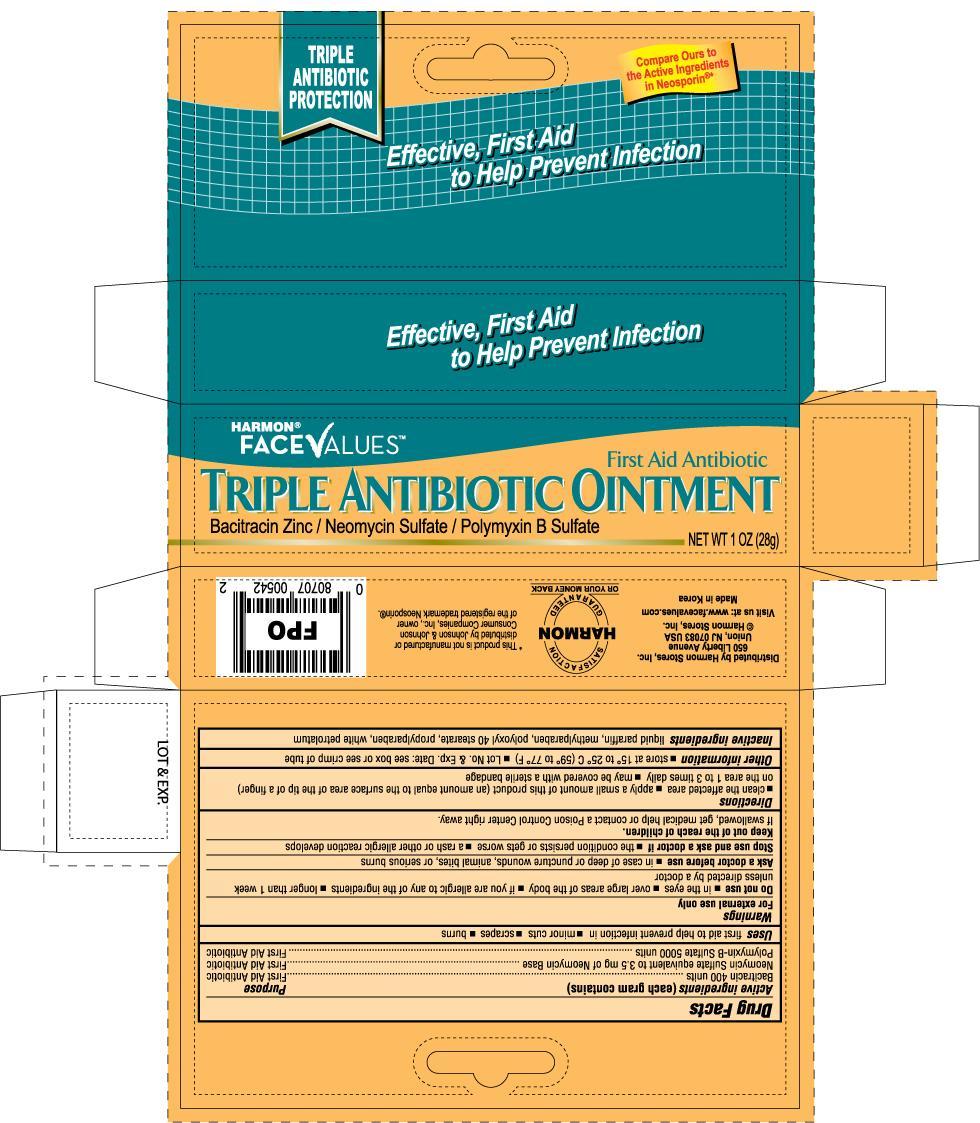 DRUG LABEL: FACE VALUES TRIPLE ANTIBIOTIC 
NDC: 63940-542 | Form: OINTMENT
Manufacturer: HARMON STORES INC.
Category: otc | Type: HUMAN OTC DRUG LABEL
Date: 20120401

ACTIVE INGREDIENTS: BACITRACIN 400 [iU]/1 g; NEOMYCIN SULFATE 3.5 mg/1 g; POLYMYXIN B SULFATE 5000 [iU]/1 g
INACTIVE INGREDIENTS: MINERAL OIL; METHYLPARABEN; POLYOXYL 40 STEARATE; PROPYLPARABEN; PETROLATUM

Drug Facts

Active Ingredients (each gram contains) Purpose

Bacitracin 400 units ...............................................................................................First Aid Antibiotic

Neomycin Sulfate equivalent to 3.5mg of Neomycin Base..........................................First Aid Antibiotic

Polymyxin-B Sulfate 5000 units ..............................................................................First Aid Antibiotic

Uses

first aid to help prevent infection in

- minor cuts
- scrapes
- burns

Warnings

For external use only

Do not use

- in the eyes
- if you are allergic to any of the ingredients
- over large areas of the body
- longer than 1 week unless directed by a doctor

Ask a doctor before use in case of deep or puncture wounds, animal bites, or serious burns

Stop use and ask a doctor if

- the condition persists or gets worse
- a rash or other allergic reaction develops

Keep out of reach of children. If swallowed, get medical help or contact a Poison Control Center right away

Directions

- clean the affected area
- apply a small amount of this product (an amount equal to the surface area of the tip of a finger) on the area 1 to 3 times daily
- may be covered with a sterile bandage

Other information

- store at 15o to 25oC (59o to 77oF)
- Lot No. and Exp. Date: see box or see crimp of tube

Inactive ingredients

liquid paraffin, white petrolatum, polyoxyl 40 stearate, methyl parahydroxybenzoate, propyl parahydroxybenzoate, purified water

DOSAGE AND ADMINISTRATION

Distributed by Harmon Stores, Inc.

650 Liberty Avenue

Union, NJ 07083 USA

www.facevalues.com

Made in Korea

PACKAGE LABEL

Enter section text here